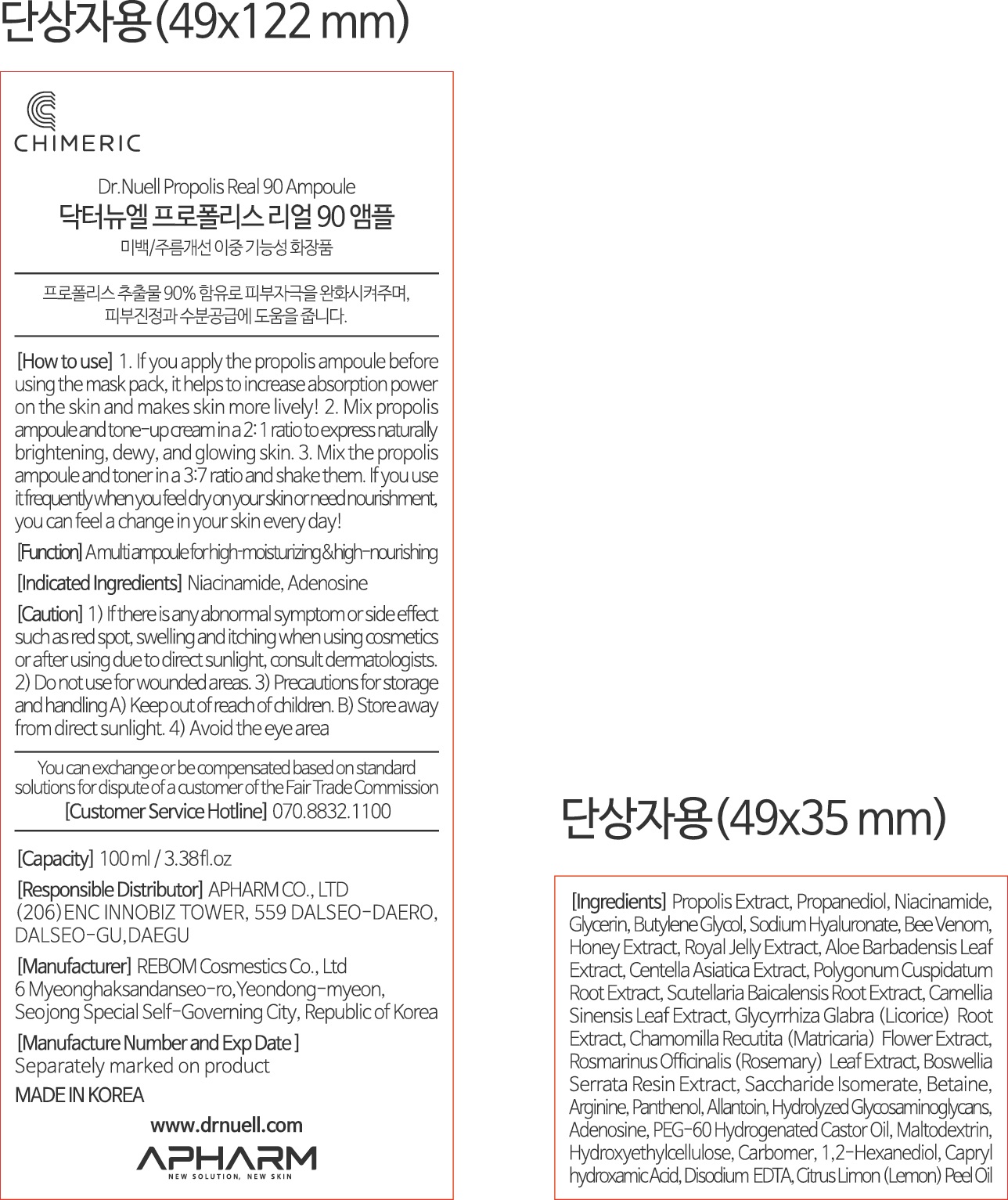 DRUG LABEL: Dr.NUELL Propolis Real 90 Ampoule
NDC: 73430-0004 | Form: LIQUID
Manufacturer: Apharm Co., Ltd.
Category: otc | Type: HUMAN OTC DRUG LABEL
Date: 20191103

ACTIVE INGREDIENTS: GLYCERIN 1 g/100 mL
INACTIVE INGREDIENTS: ALLANTOIN; BUTYLENE GLYCOL

ACTIVE INGREDIENT

glycerin

PURPOSE

a multi ampoule for high-moisturizing & high-nourishing

Keep out of reach of children

INDICATIONS AND USAGE

Please refer to the instructions on the package.

WARNINGS

1) if there is any abnormal symptom or side effect, such as red spot, swelling and itching when using cosmetlcs or after using due to direct sunlight, consult dermatologists
2) Do not use for wounded areas
3) Precautions for storage and handling
keep out of reach of children, store away from direct sunlight
4) avoid the eye area

INACTIVE INGREDIENT

butylene glycol, sodium hyaluronate, arginine, etc

DOSAGE AND ADMINISTRATION

For external use only